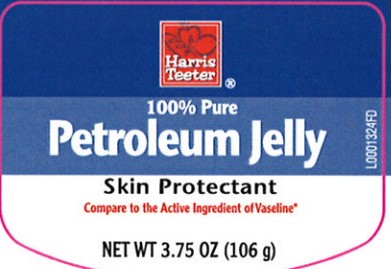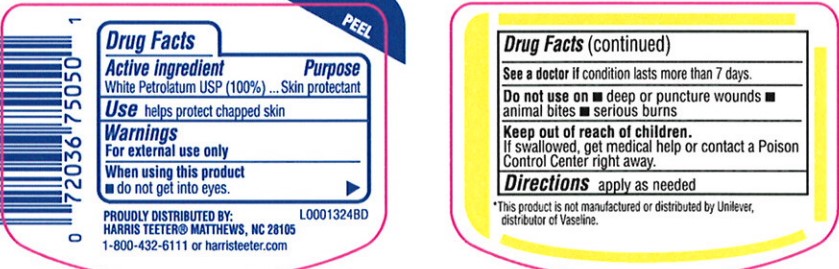 DRUG LABEL: Petroleum
NDC: 72036-069 | Form: JELLY
Manufacturer: Harris Teeter
Category: otc | Type: HUMAN OTC DRUG LABEL
Date: 20260204

ACTIVE INGREDIENTS: PETROLATUM 1 g/1 g

Harris Teeter 069.001/069AA
Petroleum Jelly

Active ingredients

White Petrolatum USP (100%)

Purpose

Skin Protectant

Uses

helps protect chapped skin

Warnings

For external use only

When using this product

- do not get into eyes

Stop use and ask a doctor

if condition lasts more than 7 days.

Do not use on

- deep or puncture wounds
- animal bites
- serious burns

Keep out of reach of children

If swallowed, get medical help or contact a Poison Control Center right away.

Directions

Apply as needed

Inactive Ingredients

None

Disclaimer

*This product is not manufactured or distributed by Unilever, distributor of Vaseline.

Adverse reaction

PROUDLY DISTRIBUTED BY:

HARRIS TEETER® MATTHEWS, NC 28105

1-800-432-6111 or harristeeter.com

principal display panel

Harris

Teeter®

100% Pure

Petroleum Jelly

Skin Protectant

Compare to the Active Ingredient of Vaseline*

NET WT 3.75 OZ (106 g)